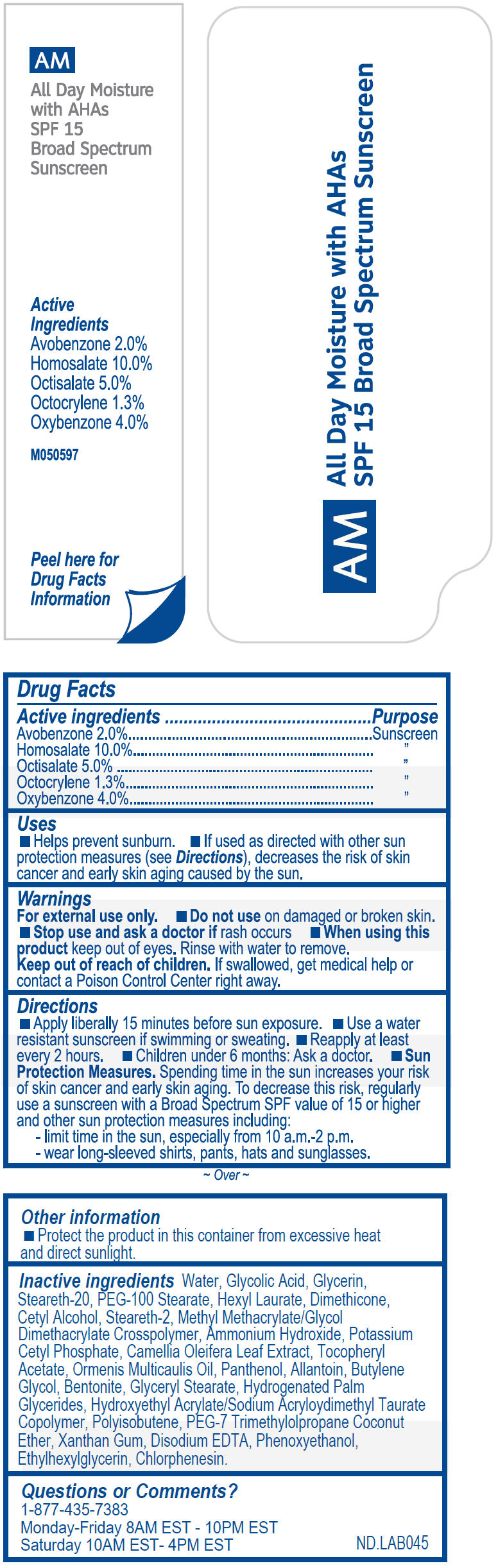 DRUG LABEL: Jane Seymour Natural Advantage AM SPF 15 All Day Moisture with AHAs
NDC: 70605-026 | Form: CREAM
Manufacturer: Guthy-Renker,LLC
Category: otc | Type: HUMAN OTC DRUG LABEL
Date: 20251201

ACTIVE INGREDIENTS: Avobenzone 2 mg/100 mL; Homosalate 10 mg/100 mL; Octisalate 5 mg/100 mL; Octocrylene 1.3 mg/100 mL; Oxybenzone 4 mg/100 mL
INACTIVE INGREDIENTS: Water; Glycolic Acid; Glycerin; AMMONIA; Steareth-20; PEG-100 Stearate; Hexyl Laurate; Dimethicone; Steareth-2; Cetyl Alcohol; CHAMOMILE FLOWER OIL; .ALPHA.-TOCOPHEROL ACETATE, DL-; Allantoin; Panthenol; Butylene Glycol; METHYL METHACRYLATE/GLYCOL DIMETHACRYLATE CROSSPOLYMER; GLYCERYL MONOSTEARATE; POTASSIUM CETYL PHOSPHATE; HYDROGENATED PALM GLYCERIDES; Xanthan Gum; EDETATE DISODIUM; CAMELLIA OLEIFERA LEAF; BENTONITE; Phenoxyethanol; Ethylhexylglycerin; CHLORPHENESIN

Jane Seymour Natural Advantage AM SPF 15 All Day Moisture with AHAs

Drug Fact Label

Active ingredient

Avobenzone - 2.0%
Homosalate - 10.0%
Octisalate - 5.0%
Octocrylene - 1.3%
Oxybenzone - 4.0%

Purpose

Sunscreen

Use

- Helps prevents sunburn.
- If used as directed with other sun protection measures (see Directions), decreases the risk of skin cancer and early skin aging caused by the sun.

Warnings

For external use only

- Do not use on damaged or broken skin.

- Stop use and ask a doctor if rash occurs

- When using this product keep out of eye. Rinse with water to remove.

- Keep out of reach of children. If swallowed, get medical help or contact a Poison Control Center right away.

Directions

- Apply liberally 15 minutes before sun exposure.
- Use a water resistant sunscreen if swimming or sweating.
- Reapply at least every 2 hours.
- Children under 6 months: Ask a doctor.
- Sun Protection Measures. Spending time in the sun increases your risk of skin cancer and early skin aging. To decrease this risk, regularly use a sunscreen with a Broad Spectrum SPF value of 15 or higher and other sun protection measures including:
  - Limit time in the sun, especially from 10 a.m.-2p.m.
  - Wear long-sleeved shirts, pants, hats and sunglasses.

Other information

- Protect the product in this container from excessive heat and direct sunlight.

Inactive ingredients

Water, Glycolic Acid, Glycerin, Steareth-20, PEG-100 Stearate, Hexyl Laurate, Dimethicone, Cetyl Alcohol, Steareth-2, Methyl Methacrylate/Glycol Dimethacrylate Crosspolymer, Ammonium Hydroxide, Potassium Cetyl Phosphate, Camellia Oleifera Leaf Extract, Tocopheryl Acetate, Ormenis Multicaulis Oil, Panthenol, Allantoin, Butylene Glycol, Bentonite, Glyceryl Stearate, Hydrogenated Palm Glycerides, Hydroxyethyl Acrylate/Sodium Acryloydimethyl Taurate Copolymer, Polyisobutene, PEG-7 Trimethylolpropane Coconut Ether, Xanthan Gum, Disodium EDTA, Phenoxyethanol, Ethylhexylglycerin, Chlorphenesin

Questions or comments?

1-877-435-7383

PRINCIPAL DISPLAY PANEL - Tube Label

AM

All Day Moisture
with AHAs
SPF 15
Broad Spectrum
Sunscreen

Active
Ingredients
Avobenzone 2.0%
Homosalate 10.0%
Octisalate 5.0%
Octocrylene 1.3%
Oxybenzone 4.0%

M050597

Peel here for
Drug Facts
Information